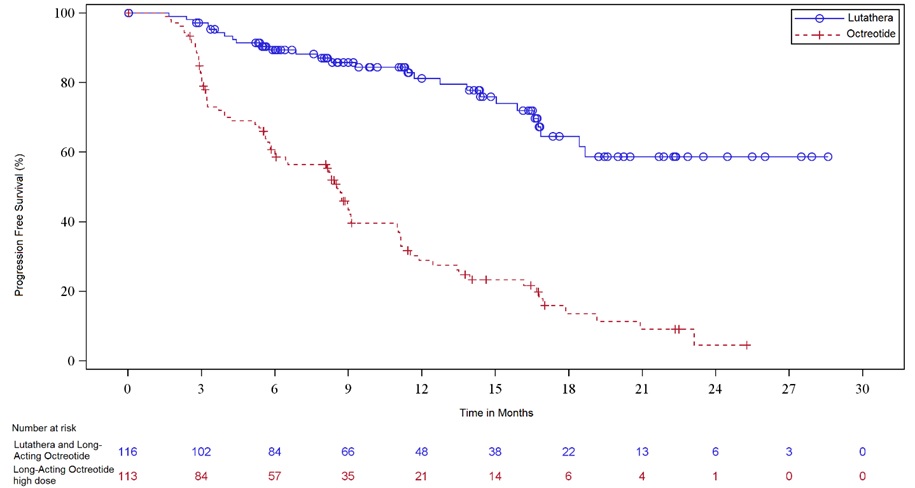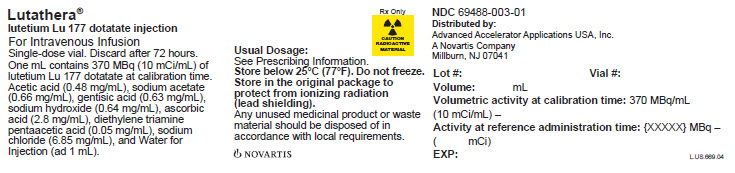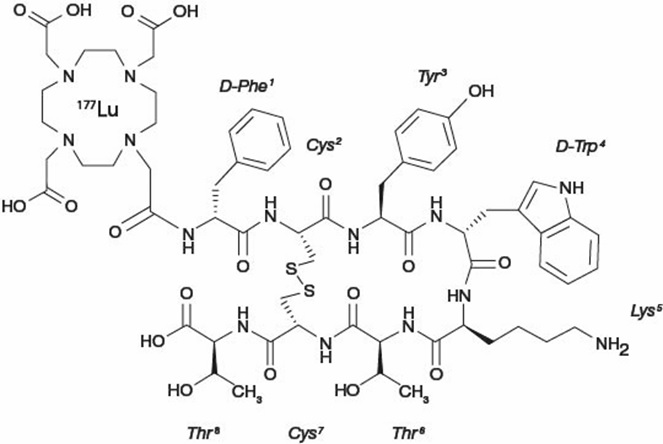 DRUG LABEL: Lutathera
NDC: 69488-003 | Form: INJECTION
Manufacturer: Advanced Accelerator Applications USA, Inc
Category: prescription | Type: HUMAN PRESCRIPTION DRUG LABEL
Date: 20260115

ACTIVE INGREDIENTS: LUTETIUM OXODOTREOTIDE LU-177 10 mCi/1 mL
INACTIVE INGREDIENTS: ACETIC ACID; SODIUM ACETATE; GENTISIC ACID; SODIUM HYDROXIDE; PENTETIC ACID; SODIUM CHLORIDE; ASCORBIC ACID; WATER

HIGHLIGHTS OF PRESCRIBING INFORMATION

These highlights do not include all the information needed to use LUTATHERA safely and effectively. See full prescribing information for LUTATHERA.
LUTATHERA® (lutetium Lu 177 dotatate) injection, for intravenous use
Initial U.S. Approval: 2018

RECENT MAJOR CHANGES

Indications and Usage (1) | 4/2024
Dosage and Administration (2.2, 2.5, 2.6) | 4/2024
Warnings and Precautions (5.1) | 4/2024

1 INDICATIONS AND USAGE

LUTATHERA is a radiolabeled somatostatin analog indicated for the treatment of adult and pediatric patients 12 years and older with somatostatin receptor-positive gastroenteropancreatic neuroendocrine tumors (GEP-NETs), including foregut, midgut, and hindgut neuroendocrine tumors.

2 DOSAGE AND ADMINISTRATION

- Verify pregnancy status of females of reproductive potential prior to initiating LUTATHERA. (2.1)
- Administer 7.4 GBq (200 mCi) every 8 weeks (± 1 week) for a total of 4 doses. (2.2)
- Administer long-acting octreotide 30 mg intramuscularly 4 to 24 hours after each LUTATHERA dose and short-acting octreotide for symptomatic management. (2.3)
- Continue long-acting octreotide 30 mg intramuscularly every 4 weeks after completing LUTATHERA until disease progression or for 18 months following treatment initiation. (2.3)
- Administer antiemetics before recommended amino acid solution. (2.3)
- Initiate recommended intravenous amino acid solution 30 minutes before LUTATHERA infusion; continue during and for at least 3 hours after LUTATHERA infusion. Do not decrease dose of amino acid solution if LUTATHERA dose is reduced. (2.3)

3 DOSAGE FORMS AND STRENGTHS

Injection: 370 MBq/mL (10 mCi/mL) in single-dose vial. (3)

4 CONTRAINDICATIONS

None. (4)

5 WARNINGS AND PRECAUTIONS

- Risk From Radiation Exposure: Minimize radiation exposure during and after treatment with LUTATHERA consistent with institutional good radiation safety practices and patient management procedures. (2.1, 5.1)
- Myelosuppression: Monitor blood cell counts. Withhold dose, reduce dose, or permanently discontinue based on the severity. (2.4, 5.2)
- Secondary Myelodysplastic Syndrome (MDS) and Leukemia: Median time to onset: MDS is 29 months; acute leukemia is 55 months. (5.3)
- Renal Toxicity: Advise patients to hydrate and to urinate frequently before, on the day of and the day after administration of LUTATHERA. Monitor serum creatinine and calculated creatinine clearance. Withhold dose, reduce dose, or permanently discontinue based on the severity. (2.3, 2.4, 5.4)
- Hepatotoxicity: Monitor transaminases, bilirubin, serum albumin and INR. (2.4, 5.5)
- Hypersensitivity Reactions: Monitor patients closely for signs and symptoms of hypersensitivity reactions, including anaphylaxis. Permanently discontinue LUTATHERA based on severity. (2.3, 2.4, 5.6)
- Neuroendocrine Hormonal Crisis: Monitor for flushing, diarrhea, hypotension, bronchoconstriction or other signs and symptoms. (5.7)
- Embryo-Fetal Toxicity: Can cause fetal harm. Advise females and males of reproductive potential of the potential risk to a fetus and to use effective contraception. (5.8, 8.1, 8.3)
- Risk of Infertility: LUTATHERA may cause infertility. (5.9, 8.3)

6 ADVERSE REACTIONS

Most common Grade 3-4 adverse reactions (≥ 4% with a higher incidence in LUTATHERA arm) are lymphopenia, increased GGT, vomiting, nausea, increased AST, increased ALT, hyperglycemia and hypokalemia. (6.1)

To report SUSPECTED ADVERSE REACTIONS, contact Novartis Pharmaceuticals Corporation at 1-888-669-6682 or FDA at 1-800-FDA-1088 or www.fda.gov/medwatch.

7 DRUG INTERACTIONS

Somatostatin Analogs: Discontinue long-acting analogs at least 4 weeks and short-acting octreotide at least 24 hours prior to each LUTATHERA dose. (2.3, 7.1)

8 USE IN SPECIFIC POPULATIONS

Lactation: Advise not to breastfeed. (8.2)

FULL PRESCRIBING INFORMATION

1 INDICATIONS AND USAGE

LUTATHERA is indicated for the treatment of adult and pediatric patients 12 years and older with somatostatin receptor-positive gastroenteropancreatic neuroendocrine tumors (GEP-NETs), including foregut, midgut, and hindgut neuroendocrine tumors.

2 DOSAGE AND ADMINISTRATION

2.1 Important Safety Instructions

LUTATHERA is a radiopharmaceutical; handle with appropriate safety measures to minimize radiation exposure [see Warnings and Precautions (5.1)]. Use waterproof gloves and effective radiation shielding when handling LUTATHERA. Radiopharmaceuticals, including LUTATHERA, should be used by or under the control of healthcare providers who are qualified by specific training and experience in the safe use and handling of radiopharmaceuticals, and whose experience and training have been approved by the appropriate governmental agency authorized to license the use of radiopharmaceuticals.

Verify pregnancy status of females of reproductive potential prior to initiating LUTATHERA [see Use in Specific Populations (8.1, 8.3)].

Monitor patients closely for signs and symptoms of hypersensitivity reactions during and following the LUTATHERA administration for a minimum of 2 hours in a setting where cardiopulmonary resuscitation medication and equipment are available [see Warnings and Precautions (5.6)].

2.2 Recommended Dosage

The recommended LUTATHERA dosage for adult and pediatric patients 12 years and older is 7.4 GBq (200 mCi) every 8 weeks (± 1 week) for a total of 4 doses. Administer premedications and concomitant medications as recommended [see Dosage and Administration (2.3)].

2.3 Premedications and Concomitant Medications

Somatostatin Analogs

- Before initiating LUTATHERA treatment: Discontinue long-acting somatostatin analogs (e.g., long-acting octreotide) at least 4 weeks prior to initiating LUTATHERA. Administer short-acting octreotide as needed; discontinue at least 24 hours prior to initiating LUTATHERA [see Drug Interactions (7.1)].
- During LUTATHERA treatment: Administer long-acting octreotide 30 mg intramuscularly between 4 to 24 hours after each LUTATHERA dose. Do not administer long-acting octreotide within 4 weeks prior to each subsequent LUTATHERA dose. Short-acting octreotide may be given for symptomatic management during LUTATHERA treatment but must be withheld at least 24 hours before each LUTATHERA dose.
- Following LUTATHERA treatment: Continue long-acting octreotide 30 mg intramuscularly every 4 weeks after completing LUTATHERA until disease progression or for 18 months following treatment initiation at the discretion of the physician.

Antiemetics

Administer antiemetics before the recommended amino acid solution.

Amino Acid Solution

Initiate an intravenous infusion of a sterile amino acid solution containing L-lysine and L-arginine (Table 1) 30 minutes before the start of the LUTATHERA infusion. Use a three-way valve to administer the amino acid solution using the same venous access as LUTATHERA or administer the amino acid solution through a separate venous access in the patient’s other arm. Continue the amino acid solution infusion during and for at least 3 hours after completion of the LUTATHERA infusion. Do not decrease the dose of the amino acid solution if a reduced dose of LUTATHERA is administered [see Warnings and Precautions (5.4)].

Table 1. Amino Acid Solution
Item | Specification
L-lysine HCl | Between 18 and 25 ga
L-arginine HCl | Between 18 and 25 gb
Volume | 1 to 2 L
Osmolality | < 1200 mOsmol/kg
aequivalent to 14.4 to 20 g L-lysine.
bequivalent to 14.9 to 20.7 g L-arginine.

Hypersensitivity Prophylaxis

Premedicate patients who have had prior Grade 1 or 2 hypersensitivity reactions to LUTATHERA. Do not re-challenge patients who experience Grade 3 or 4 hypersensitivity reactions to LUTATHERA [see Warnings and Precautions (5.6)].

2.4 Dosage Modifications for Adverse Reactions

Recommended dose modifications of LUTATHERA for adverse reactions are provided in Table 2.

Table 2. Recommended Dosage Modifications of LUTATHERA for Adverse Reactions
Adverse reaction | Severity of adverse reactiona | Dose modification
Thrombocytopenia [see Warnings and Precautions (5.2)] | First occurrence of Grade 2, 3, or 4 | Withhold dose until complete or partial resolution (Grade 0 to 1).; Resume LUTATHERA at 3.7 GBq (100 mCi) in patients with complete or partial resolution. If reduced dose does not result in Grade 2, 3, or 4 thrombocytopenia, administer LUTATHERA at 7.4 GBq (200 mCi) as next dose.; Permanently discontinue LUTATHERA for Grade 2 or higher thrombocytopenia requiring a dosing interval beyond 16 weeks.
Thrombocytopenia [see Warnings and Precautions (5.2)] | Recurrent Grade 2, 3, or 4 | Permanently discontinue LUTATHERA.
Anemia and Neutropenia [see Warnings and Precautions (5.2)] | First occurrence of Grade 3 or 4 | Withhold dose until complete or partial resolution (Grade 0, 1, or 2).; Resume LUTATHERA at 3.7 GBq (100 mCi) in patients with complete or partial resolution. If reduced dose does not result in Grade 3 or 4 anemia or neutropenia, administer LUTATHERA at 7.4 GBq (200 mCi) as next dose.; Permanently discontinue LUTATHERA for Grade 3 or higher anemia or neutropenia requiring a dosing interval beyond 16 weeks.
Anemia and Neutropenia [see Warnings and Precautions (5.2)] | Recurrent Grade 3 or 4 | Permanently discontinue LUTATHERA.
Renal Toxicity [see Warnings and Precautions (5.4)] | First occurrence of:; - Creatinine clearance less than 40 mL/min; calculated using Cockcroft-Gault formula with actual body weight, or - 40% increase from baseline serum creatinine, or - 40% decrease from baseline creatinine clearance; calculated using Cockcroft-Gault formula with actual body weight. | Withhold dose until resolution or return to baseline.; Resume LUTATHERA at 3.7 GBq (100 mCi) in patients with resolution or return to baseline. If reduced dose does not result in renal toxicity, administer LUTATHERA at 7.4 GBq (200 mCi) as next dose.; Permanently discontinue LUTATHERA for renal toxicity requiring a dosing interval beyond 16 weeks.
Renal Toxicity [see Warnings and Precautions (5.4)] | Recurrent renal toxicity | Permanently discontinue LUTATHERA.
Hepatotoxicity [see Warnings and Precautions (5.5)] | First occurrence of:; - Bilirubinemia greater than 3 times the upper limit of normal (Grade 3 or 4), or - Serum albumin less than 30 g/L with international normalized ratio (INR) > 1.5. | Withhold dose until resolution or return to baseline.; Resume LUTATHERA at 3.7 GBq (100 mCi) in patients with resolution or return to baseline. If reduced LUTATHERA dose does not result in hepatotoxicity, administer LUTATHERA at 7.4 GBq (200 mCi) as next dose.; Permanently discontinue LUTATHERA for hepatotoxicity requiring a dosing interval beyond 16 weeks.
Hepatotoxicity [see Warnings and Precautions (5.5)] | Recurrent hepatotoxicity | Permanently discontinue LUTATHERA.
Hypersensitivity Reactionsb [see Warnings and Precautions (5.6)] | First occurrence of Grade 3 or 4 | Permanently discontinue LUTATHERA.
Any Other Adverse Reactionsc [see Adverse Reactions (6.1)] | First occurrence of Grade 3 or 4 | Withhold dose until complete or partial resolution (Grade 0 to 2).; Resume LUTATHERA at 3.7 GBq (100 mCi) in patients with complete or partial resolution. If reduced dose does not result in Grade 3 or 4 toxicity, administer LUTATHERA at 7.4 GBq (200 mCi) as next dose.; Permanently discontinue LUTATHERA for Grade 3 or higher adverse reactions requiring a dosing interval beyond 16 weeks.
Any Other Adverse Reactionsc [see Adverse Reactions (6.1)] | Recurrent Grade 3 or 4 | Permanently discontinue LUTATHERA.
aGrading of severity is defined in the most current Common Terminology Criteria for Adverse Events (CTCAE).
bIncluding allergic reaction and anaphylaxis.
cNo dose modification required for hematological toxicities Grade 3 or Grade 4 solely due to lymphopenia.

2.5 Preparation and Administration

Preparation Instructions

- Use aseptic technique and radiation shielding when handling or administering the LUTATHERA solution. Use tongs when handling the vial to minimize radiation exposure.
- Inspect the product visually under a shielded screen for particulate matter and discoloration prior to administration. Discard the vial if particulates and/or discoloration are present.
- Do not inject the LUTATHERA solution directly into any other intravenous solution.
- Confirm the amount of radioactivity of LUTATHERA delivered to the patient with an appropriate dose calibrator prior to and after each LUTATHERA administration.
- Dispose of any unused medicinal product or waste material in accordance with local and federal laws.

Administration Instructions

- Prior to administration, flush the intravenous catheter used for LUTATHERA administration with ≥ 10 mL of 0.9% Sodium Chloride Injection, USP to ensure patency and to minimize the risk of extravasation. Manage cases of extravasation as per institutional guidelines.
- The gravity method, peristaltic pump method, or the syringe pump method may be used for the administration of the recommended dosage. Do not administer LUTATHERA as an intravenous bolus.
- When using the gravity or peristaltic pump method, infuse LUTATHERA directly from its original container.
- Use the peristaltic pump or syringe pump method when administering a reduced dose of LUTATHERA following a dosage modification for an adverse reaction. When using the gravity method for a reduced dose, adjust the LUTATHERA dose before the administration to avoid the delivery of an incorrect volume of LUTATHERA.

Intravenous Methods of Administration

Instructions for the Gravity Method

- Insert a 2.5 cm, 20-gauge needle (short needle) into the LUTATHERA vial and connect via a catheter to 500 mL 0.9% Sodium Chloride Injection, USP (used to transport the LUTATHERA solution during the infusion). Ensure that the short needle does not touch the LUTATHERA solution in the vial and do not connect this short needle directly to the patient. Do not allow the 0.9% Sodium Chloride Injection, USP to flow into the LUTATHERA vial prior to the initiation of the LUTATHERA infusion and do not inject the LUTATHERA solution directly into the 0.9% Sodium Chloride Injection, USP.
- Insert a second needle that is 9 cm, 18-gauge (long needle) into the LUTATHERA vial ensuring that this long needle touches and is secured to the bottom of the LUTATHERA vial during the entire infusion. Connect the long needle to the patient by an intravenous catheter that is pre-filled with 0.9% Sodium Chloride Injection, USP and that is used for the LUTATHERA infusion into the patient.
- Use a clamp or an infusion pump to regulate the flow of the 0.9% Sodium Chloride Injection, USP via the short needle into the LUTATHERA vial at a rate of 50 mL/hour to 100 mL/hour for 5 to 10 minutes and then 200 mL/hour to 300 mL/hour for an additional 25 to 30 minutes (the 0.9% Sodium Chloride Injection, USP entering the vial through the short needle will carry the LUTATHERA solution from the vial to the patient via the intravenous catheter connected to the long needle over a total duration of 30 to 40 minutes).
- During the infusion, ensure that the level of solution in the LUTATHERA vial remains constant.
- Disconnect the vial from the long needle line and clamp the 0.9% Sodium Chloride Injection, USP line once the level of radioactivity is stable for at least five minutes.
- Follow the infusion with an intravenous flush of 25 mL of 0.9% Sodium Chloride Injection, USP through the intravenous catheter to the patient.

Instructions for the Peristaltic Pump Method

- Insert a filtered 2.5 cm, 20-gauge needle (short venting needle) into the LUTATHERA vial. Ensure that the short needle does not touch the LUTATHERA solution in the vial and do not connect this short needle directly to the patient or to the peristaltic pump.
- Insert a second needle that is 9 cm, 18 gauge (long needle) into the LUTATHERA vial ensuring that the long needle touches and is secured to the bottom of the LUTATHERA vial during the entire infusion. Connect the long needle and a 0.9% Sodium Chloride Injection, USP to a 3-way stopcock valve via appropriate tubing.
- Connect the output of the 3-way stopcock valve to tubing installed on the input side of the peristaltic pump according to manufacturer’s instructions.
- Prime the line by opening the 3-way stopcock valve and pumping the LUTATHERA solution through the tubing until it reaches the exit of the valve.
- Prime the intravenous catheter that will be connected to the patient by opening the 3-way stopcock valve to the 0.9% Sodium Chloride Injection, USP and pumping the 0.9% Sodium Chloride Injection, USP until it exits the end of the catheter tubing.
- Connect the primed intravenous catheter to the patient and set the 3-way stopcock valve such that the LUTATHERA solution is in line with the peristaltic pump.
- Infuse an appropriate volume of LUTATHERA solution over a 30-40 min period to deliver the desired radioactivity.
- When the desired LUTATHERA radioactivity has been delivered, stop the peristaltic pump and then change the position of the 3-way stopcock valve so that the peristaltic pump is in line with the 0.9% Sodium Chloride Injection, USP. Restart the peristaltic pump and infuse an intravenous flush of 25 mL of 0.9% Sodium Chloride Injection, USP through the intravenous catheter to the patient.

Instructions for the Syringe Pump Method

- Withdraw an appropriate volume of LUTATHERA solution to deliver the desired radioactivity by using a disposable syringe fitted with a syringe shield and a disposable sterile needle that is 9 cm, 18 gauge (long needle). To aid the withdrawal of the solution, a filtered 2.5 cm, 20-gauge needle (short venting needle) can be used to reduce the resistance from the pressurized vial. Ensure that the short needle does not touch the LUTATHERA solution in the vial.
- Fit the syringe into the shielded pump and include a 3-way stopcock valve between the syringe and an intravenous catheter pre-filled with 0.9% Sodium Chloride Injection, USP and used for LUTATHERA administration to the patient.
- Infuse an appropriate volume of LUTATHERA solution over a 30-40 min period to deliver the desired radioactivity.
- When the desired LUTATHERA radioactivity has been delivered, stop the syringe pump and then change the position of the 3-way stopcock valve to flush the syringe with 25 mL of 0.9% Sodium Chloride Injection, USP. Restart the syringe pump.
- After the flush of the syringe has been completed, perform an intravenous flush with 25 mL of 0.9% Sodium Chloride Injection, USP through the intravenous catheter to the patient.

2.6 Radiation Dosimetry

The maximum penetration of lutetium-177 in tissue is 2.2 mm and the mean penetration is 0.67 mm.
The mean and standard deviation (SD) of the estimated radiation absorbed doses for adults receiving LUTATHERA are shown in Table 3. The mean and SD of the estimated radiation absorbed doses for pediatric patients 12 years and older receiving LUTATHERA are shown in Table 4.

Table 3. Estimated Radiation Absorbed Dose for LUTATHERA in Adults in NETTER-1
 | Absorbed dose per unit activity; (Gy/GBq); (N = 20) |  | Calculated absorbed dose for 4 x 7.4 GBq; (29.6 GBq cumulative activity); (Gy)
Organ | Mean | SD | Mean | SD
Adrenals | 0.037 | 0.016 | 1.1 | 0.5
Brain | 0.027 | 0.016 | 0.8 | 0.5
Breasts | 0.027 | 0.015 | 0.8 | 0.4
Gallbladder wall | 0.042 | 0.019 | 1.2 | 0.6
Heart wall | 0.032 | 0.015 | 0.9 | 0.4
Kidneys | 0.654 | 0.295 | 19.4 | 8.7
Livera | 0.299 | 0.226 | 8.9 | 6.7
Lower large intestine wall | 0.029 | 0.016 | 0.9 | 0.5
Lungs | 0.031 | 0.015 | 0.9 | 0.4
Muscle | 0.029 | 0.015 | 0.8 | 0.4
Osteogenic cells | 0.151 | 0.268 | 4.5 | 7.9
Ovariesb | 0.031 | 0.013 | 0.9 | 0.4
Pancreas | 0.038 | 0.016 | 1.1 | 0.5
Red marrowc | 0.035 | 0.029 | 1.0 | 0.8
Skin | 0.027 | 0.015 | 0.8 | 0.4
Small intestine | 0.031 | 0.015 | 0.9 | 0.5
Spleen | 0.846 | 0.804 | 25.1 | 23.8
Stomach wall | 0.032 | 0.015 | 0.9 | 0.5
Testesd | 0.026 | 0.018 | 0.8 | 0.5
Thymus | 0.028 | 0.015 | 0.8 | 0.5
Thyroid | 0.027 | 0.016 | 0.8 | 0.5
Total body | 0.052 | 0.027 | 1.6 | 0.8
Upper large intestine wall | 0.032 | 0.015 | 0.9 | 0.4
Urinary bladder wall | 0.437 | 0.176 | 12.8 | 5.3
Uterusb | 0.032 | 0.013 | 1.0 | 0.4
aN = 18 (two patients excluded because the liver absorbed dose was biased by the uptake of the liver metastases).
bN = 9 (female patients only).
cRed marrow dosimetry estimates were determined using blood radioactivity.
dN = 11 (male patients only).

Table 4. Estimated Radiation Absorbed Dose for LUTATHERA in Pediatric Patients 12 Years and Older in NETTER-P
 | Absorbed dose per unit activity; (Gy/GBq); (N = 8a) |  | Calculated absorbed dose for 4 x 7.4 GBq; (29.6 GBq cumulative activity); (Gy)
Organ | Mean | SD | Mean | SD
Adrenals | 0.045 | 0.011 | 1.3 | 0.3
Brain | 0.021 | 0.006 | 0.6 | 0.2
Breastsb | 0.018 | 0.006 | 0.5 | 0.2
Esophagus | 0.024 | 0.006 | 0.7 | 0.2
Eyes | 0.021 | 0.006 | 0.6 | 0.2
Gallbladder wall | 0.031 | 0.011 | 0.9 | 0.3
Heart wall | 0.024 | 0.006 | 0.7 | 0.2
Kidneys | 0.773 | 0.288 | 22.9 | 8.5
Left colon | 0.265 | 0.081 | 7.8 | 2.4
Liver | 0.216 | 0.231 | 6.4 | 6.8
Lungs | 0.024 | 0.006 | 0.7 | 0.2
Osteogenic cells | 0.046 | 0.019 | 1.4 | 0.6
Ovariesb | 0.026 | 0.007 | 0.8 | 0.2
Pancreas | 0.027 | 0.007 | 0.8 | 0.2
Pituitaryc | 1.053 | 0.348 | 31.2 | 10.3
Prostated | 0.026 | 0.006 | 0.8 | 0.2
Rectum | 0.272 | 0.085 | 8.0 | 2.5
Red marrow (blood)e | 0.027 | 0.005 | 0.8 | 0.2
Red marrow (image) e | 0.055 | 0.026 | 1.6 | 0.8
Right colon | 0.152 | 0.045 | 4.5 | 1.3
Salivary glands | 0.036 | 0.017 | 1.1 | 0.5
Small intestine | 0.046 | 0.013 | 1.3 | 0.4
Spleen | 0.733 | 0.304 | 21.7 | 9.0
Stomach wall | 0.027 | 0.007 | 0.8 | 0.2
Testesd | 0.021 | 0.005 | 0.6 | 0.2
Thymus | 0.022 | 0.006 | 0.7 | 0.2
Thyroid | 0.022 | 0.006 | 0.6 | 0.2
Total body | 0.042 | 0.010 | 1.2 | 0.3
Urinary bladder wall | 0.573 | 0.088 | 17.0 | 2.6
Uterusb | 0.031 | 0.008 | 0.9 | 0.2
aData are pooled for 8 pediatric patients with somatostatin receptor-positive (SSTR+) tumors, including 4 patients with GEP-NETs.
bN = 5 (female patients only).
cN = 7 (3 GEP-NET, 4 SSTR+ tumors). Pituitary dosimetry estimates were only performed when pituitary uptake was clearly observed on the planar images. Due to the small size of the pituitary gland, availability for quantification only from planar images and interference from activity in the nasal mucosa, estimates can be associated with a large uncertainty. Pituitary gland absorbed dose estimate includes absorbed dose contributions from activity within the pituitary only, dose contributions from other tissues are not included.
dN = 3 (male patients only).
eRed marrow dosimetry estimates were determined either using blood radioactivity or by imaging and scaling of a representative region of the lumbar spine.

3 DOSAGE FORMS AND STRENGTHS

Injection: 370 MBq/mL (10 mCi/mL) of lutetium Lu 177 dotatate as a clear and colorless to slightly yellow solution in a single-dose vial.

4 CONTRAINDICATIONS

None.

5 WARNINGS AND PRECAUTIONS

5.1 Risk From Radiation Exposure

LUTATHERA contributes to a patient’s overall long-term cumulative radiation exposure. Long-term cumulative radiation exposure is associated with an increased risk for cancer. These risks of radiation associated with the use of LUTATHERA are greater in pediatric patients than in adults [see Use in Specific Populations (8.4)].

Radiation can be detected in the urine for up to 30 days following LUTATHERA administration. Minimize radiation exposure to patients, medical personnel, and household contacts during and after treatment with LUTATHERA consistent with institutional good radiation safety practices, patient management procedures, Nuclear Regulatory Commission patient-release guidance, and instructions to the patient for follow-up radiation protection at home [see Dosage and Administration (2.1), Clinical Pharmacology (12.3)].

5.2 Myelosuppression

In NETTER-1, myelosuppression occurred more frequently in patients receiving LUTATHERA with long-acting octreotide compared to patients receiving high-dose long-acting octreotide (all Grades/Grade 3 or 4): anemia (81%/0) versus (54%/1%); thrombocytopenia (53%/1%) versus (17%/0); and neutropenia (26%/3%) versus (11%/0). In NETTER-1, platelet nadir occurred at a median of 5.1 months following the first dose. Of the 59 patients who developed thrombocytopenia, 68% had platelet recovery to baseline or normal levels. The median time to platelet recovery was 2 months. Fifteen of the nineteen patients in whom platelet recovery was not documented had post-nadir platelet counts. Among these 15 patients, 5 improved to Grade 1, 9 to Grade 2, and 1 to Grade 3.

Monitor blood cell counts. Withhold dose, reduce dose, or permanently discontinue LUTATHERA based on the severity of myelosuppression [see Dosage and Administration (2.4)].

5.3 Secondary Myelodysplastic Syndrome and Leukemia

In NETTER-1, with a median follow-up time of 76 months in the main study, myelodysplastic syndrome (MDS) was reported in 2.3% of patients receiving LUTATHERA with long-acting octreotide compared to no patients receiving high-dose long-acting octreotide.

In ERASMUS, 16 patients (2.0%) developed MDS and 4 (0.5%) developed acute leukemia. The median time to onset was 29 months (9 to 45 months) for MDS and 55 months (32 to 125 months) for acute leukemia.

5.4 Renal Toxicity

In ERASMUS, 8 patients (< 1%) developed renal failure 3 to 36 months following LUTATHERA. Two of these patients had underlying renal impairment or risk factors for renal failure (e.g., diabetes or hypertension) and required dialysis.

Administer the recommended amino acid solution before, during and after LUTATHERA [see Dosage and Administration (2.3)] to decrease the reabsorption of lutetium Lu 177 dotatate through the proximal tubules and decrease the radiation dose to the kidneys. Advise patients to hydrate and to urinate frequently before, on the day of, and the day after administration of LUTATHERA.

Monitor serum creatinine and calculated creatinine clearance. Withhold dose, reduce dose, or permanently discontinue LUTATHERA based on the severity of renal toxicity [see Dosage and Administration (2.4)].

Patients with baseline renal impairment may be at increased risk of toxicity due to increased radiation exposure [see Use in Specific Populations (8.6)].

5.5 Hepatotoxicity

In ERASMUS, 2 patients (< 1%) were reported to have hepatic tumor hemorrhage, edema, or necrosis, with one patient experiencing intrahepatic congestion and cholestasis. Patients with hepatic metastasis may be at increased risk of hepatotoxicity due to radiation exposure.

Monitor transaminases, bilirubin, serum albumin, and international normalized ratio (INR) during treatment. Withhold dose, reduce dose, or permanently discontinue LUTATHERA based on the severity of hepatotoxicity [see Dosage and Administration (2.4)].

5.6 Hypersensitivity Reactions

Hypersensitivity reactions, including angioedema, occurred in patients treated with LUTATHERA [see Adverse Reactions (6.2)]. Monitor patients closely for signs and symptoms of hypersensitivity reactions, including anaphylaxis, during and following LUTATHERA administration for a minimum of 2 hours in a setting where cardiopulmonary resuscitation medication and equipment are available. Discontinue the infusion upon the first observation of any signs or symptoms consistent with a severe hypersensitivity reaction and initiate appropriate therapy.

Premedicate patients with a history of Grade 1 or 2 hypersensitivity reactions to LUTATHERA before subsequent doses [see Dosage and Administration (2.3)]. Permanently discontinue LUTATHERA in patients who experience Grade 3 or 4 hypersensitivity reactions [see Dosage and Administration (2.4)].

5.7 Neuroendocrine Hormonal Crisis

Neuroendocrine hormonal crises, manifesting with flushing, diarrhea, bronchospasm and hypotension, occurred in < 1% of patients in ERASMUS and typically occurred during or within 24 hours following the initial LUTATHERA dose. Two (< 1%) patients were reported to have hypercalcemia.

Monitor patients for flushing, diarrhea, hypotension, bronchoconstriction or other signs and symptoms of tumor-related hormonal release. Administer intravenous somatostatin analogs, fluids, corticosteroids, and electrolytes as indicated.

5.8 Embryo-Fetal Toxicity

Based on its mechanism of action, LUTATHERA can cause fetal harm when administered to a pregnant woman [see Clinical Pharmacology (12.1)]. There are no available data on LUTATHERA use in pregnant women. No animal studies using lutetium Lu 177 dotatate have been conducted to evaluate its effect on female reproduction and embryo-fetal development; however, radioactive emissions, including those from LUTATHERA, can cause fetal harm.

Verify pregnancy status of females of reproductive potential prior to initiating LUTATHERA [see Dosage and Administration (2.1)].

Advise pregnant women of the potential risk to a fetus. Advise females of reproductive potential to use effective contraception during treatment with LUTATHERA and for 7 months after the last dose. Advise males with female partners of reproductive potential to use effective contraception during treatment with LUTATHERA and for 4 months after the last dose [see Use in Specific Populations (8.1, 8.3)].

5.9 Risk of Infertility

LUTATHERA may cause infertility in males and females. The recommended cumulative dose of 29.6 GBq of LUTATHERA results in a radiation absorbed dose to the testes and ovaries within the range where temporary or permanent infertility can be expected following external beam radiotherapy [see Dosage and Administration (2.6), Use in Specific Populations (8.3)].

6 ADVERSE REACTIONS

The following clinically significant adverse reactions are described elsewhere in the labeling:

- Myelosuppression [see Warnings and Precautions (5.2)]
- Secondary Myelodysplastic Syndrome and Leukemia [see Warnings and Precautions (5.3)]
- Renal Toxicity [see Warnings and Precautions (5.4)]
- Hepatotoxicity [see Warnings and Precautions (5.5)]
- Hypersensitivity Reactions [see Warnings and Precautions (5.6)]
- Neuroendocrine Hormonal Crisis [see Warnings and Precautions (5.7)]

6.1 Clinical Trials Experience

Because clinical trials are conducted under widely varying conditions, adverse reaction rates observed in the clinical trials of a drug cannot be directly compared to rates in the clinical trials of another drug and may not reflect the rates observed in practice.

The data in WARNINGS AND PRECAUTIONS reflect exposure to LUTATHERA in 111 patients with advanced, progressive midgut neuroendocrine tumors (NETTER-1). Safety data in WARNINGS AND PRECAUTIONS were also obtained in an additional 22 patients in a non-randomized pharmacokinetic sub-study of NETTER-1 and in a subset of patients (811 of 1214) with advanced somatostatin receptor-positive tumors enrolled in ERASMUS [see Warnings and Precautions (5)].

Adult Population

NETTER-1

The safety data of LUTATHERA with octreotide was evaluated in NETTER-1 [see Clinical Studies (14.1)]. Patients with progressive, somatostatin receptor-positive midgut carcinoid tumors received LUTATHERA 7.4 GBq (200 mCi) administered every 8 to 16 weeks concurrently with the recommended amino acid solution and with long-acting octreotide (30 mg administered by intramuscular injection within 24 hours of each LUTATHERA dose) (N = 111), or high-dose octreotide (defined as long-acting octreotide 60 mg by intramuscular injection every 4 weeks) (N = 112) [see Clinical Studies (14.1)]. Among patients receiving LUTATHERA with octreotide, 79% received a cumulative dose > 22.2 GBq (> 600 mCi) and 76% of patients received all four planned doses. Six percent (6%) of patients required a dose reduction and 13% of patients discontinued LUTATHERA. Five patients discontinued LUTATHERA for renal-related events and 4 discontinued for hematological toxicities.

Table 5 and Table 6 summarize the incidence of adverse reactions and laboratory abnormalities, respectively. The most common Grade 3-4 adverse reactions occurring with a greater frequency among patients receiving LUTATHERA with octreotide compared to patients receiving high-dose octreotide include: lymphopenia (44%), increased gamma-glutamyltransferase (GGT) (20%), vomiting (7%), nausea and increased aspartate aminotransferase (AST) (5% each), and increased alanine aminotransferase (ALT), hyperglycemia and hypokalemia (4% each).

Table 5. Adverse Reactions Occurring at Higher Incidence in Patients Receiving LUTATHERA with Long-Acting Octreotide Compared to High-Dose Long-Acting Octreotide (Between Arm Difference of ≥ 5% All Grades or ≥ 2% Grades 3-4)a
Adverse reactiona | LUTATHERA with long-acting Octreotide (30 mg) (N = 111) |  | Long-acting Octreotide (60 mg) (N = 112)
Adverse reactiona | All Grades % | Grades 3-4 % | All Grades % | Grades 3-4 %
Gastrointestinal disorders
Nausea | 65 | 5 | 12 | 2
Vomiting | 53 | 7 | 10 | 0
Abdominal pain | 26 | 3 | 19 | 3
Diarrhea | 26 | 3 | 18 | 1
Constipation | 10 | 0 | 5 | 0
General disorders
Fatigue | 38 | 1 | 26 | 2
Peripheral edema | 16 | 0 | 9 | 1
Pyrexia | 8 | 0 | 3 | 0
Metabolism and nutrition disorders
Decreased appetite | 21 | 0 | 11 | 3
Nervous system disorders
Headache | 17 | 0 | 5 | 0
Dizziness | 17 | 0 | 8 | 0
Dysgeusia | 8 | 0 | 2 | 0
Vascular disorders
Flushing | 14 | 1 | 9 | 0
Hypertension | 12 | 2 | 7 | 2
Musculoskeletal and connective tissue disorders
Back pain | 13 | 2 | 10 | 0
Pain in extremity | 11 | 0 | 5 | 0
Myalgia | 5 | 0 | 0 | 0
Neck pain | 5 | 0 | 0 | 0
Renal and urinary disorders
Renal failureb | 13 | 3 | 4 | 1
Radiation-related urinary tract adverse reactionsc | 8 | 0 | 3 | 0
Psychiatric disorders
Anxiety | 12 | 1 | 5 | 0
Skin and subcutaneous tissue disorders
Alopecia | 12 | 0 | 2 | 0
Respiratory, thoracic and mediastinal disorders
Cough | 11 | 1 | 6 | 0
Cardiac disorders
Atrial fibrillation | 5 | 1 | 0 | 0
aNational Cancer Institute Common Terminology Criteria for Adverse Events (CTCAE) Version 4.03. Only displays adverse reactions occurring at a higher incidence in LUTATHERA-treated patients [between arm difference of ≥ 5% (all Grades) or ≥ 2% (Grades 3-4)].
bIncludes the terms: Glomerular filtration rate decreased, acute kidney injury, acute prerenal failure, azotemia, renal disorder, renal failure, renal impairment.
cIncludes the terms: Dysuria, micturition urgency, nocturia, pollakiuria, renal colic, renal pain, urinary tract pain and urinary incontinence.

Table 6. Laboratory Abnormalities Occurring at Higher Incidence in Patients Receiving LUTATHERA with Long-Acting Octreotide Compared to High-Dose Long-Acting Octreotide (Between Arm Difference of ≥ 5% All Grades or ≥ 2% Grades 3-4)a,b
Laboratory abnormalityb | LUTATHERA with long-acting Octreotide (30 mg) (N = 111) |  | Long-acting Octreotide (60 mg) (N = 112)
Laboratory abnormalityb | All Grades % | Grades 3-4 % | All Grades % | Grades 3-4 %
Hematology
Lymphopenia | 90 | 44 | 39 | 5
Anemia | 81 | 0 | 55 | 1
Leukopenia | 55 | 2 | 20 | 0
Thrombocytopenia | 53 | 1 | 17 | 0
Neutropenia | 26 | 3 | 11 | 0
Renal/Metabolic
Creatinine increased | 85 | 1 | 73 | 0
Hyperglycemia | 82 | 4 | 67 | 2
Hyperuricemia | 34 | 6 | 30 | 6
Hypocalcemia | 32 | 0 | 14 | 0
Hypokalemia | 26 | 4 | 21 | 2
Hyperkalemia | 19 | 0 | 11 | 0
Hypernatremia | 17 | 0 | 7 | 0
Hypoglycemia | 15 | 0 | 8 | 0
Hepatic
GGT increased | 66 | 20 | 67 | 16
Alkaline phosphatase increased | 65 | 5 | 55 | 9
AST increased | 50 | 5 | 35 | 0
ALT increased | 43 | 4 | 34 | 0
Blood bilirubin increased | 30 | 2 | 28 | 0
aValues are worst grade observed after randomization.
bNational Cancer Institute Common Terminology Criteria for Adverse Events (CTCAE) Version 4.03. Only displays laboratory abnormalities occurring at a higher incidence in LUTATHERA-treated patients [between arm difference of ≥ 5% (all Grades) or ≥ 2% (Grades 3-4)].

ERASMUS

Safety data are available from 1214 patients in ERASMUS, an international, single-institution, single-arm, open-label trial of patients with somatostatin receptor-positive tumors (neuroendocrine and other primaries). Patients received LUTATHERA 7.4 GBq (200 mCi) administered every 6 to 13 weeks with or without octreotide. Retrospective medical record review was conducted on a subset of 811 patients to document serious adverse reactions. Eighty-one (81%) percent of patients in the subset received a cumulative dose ≥ 22.2 GBq (≥ 600 mCi). With a median follow-up time of more than 4 years, the following rates of serious adverse reactions were reported: myelodysplastic syndrome (2%), acute leukemia (1%), renal failure (2%), hypotension (1%), cardiac failure (2%), myocardial infarction (1%), and neuroendocrine hormonal crisis (1%).

Pediatric Population

NETTER-P

Safety data are available from 9 pediatric patients in NETTER-P (NCT04711135), an international, multi-center, single-arm, open-label trial of patients with somatostatin receptor-positive tumors, including 4 patients with GEP-NETs. Patients received LUTATHERA 7.4 GBq (200 mCi) administered every 8 weeks concurrently with the recommended amino acid solution. Adverse reactions observed in NETTER-P were similar to those observed in adults treated with LUTATHERA.

6.2 Postmarketing Experience

The following adverse reactions have been identified during post approval use of LUTATHERA. Because these reactions are reported voluntarily from a population of uncertain size, it is not always possible to reliably estimate their frequency or establish a causal relationship to drug exposure.

- Immune System Disorders: hypersensitivity reactions, including angioedema

7 DRUG INTERACTIONS

7.1 Somatostatin Analogs

Somatostatin and its analogs competitively bind to somatostatin receptors and may interfere with the efficacy of LUTATHERA. Discontinue long-acting somatostatin analogs at least 4 weeks and short-acting octreotide at least 24 hours prior to each LUTATHERA dose. Administer short- and long-acting octreotide during LUTATHERA treatment as recommended [see Dosage and Administration (2.3)].

7.2 Glucocorticoids

Glucocorticoids can induce down-regulation of subtype 2 somatostatin receptors (SSTR2). Avoid repeated administration of high doses of glucocorticoids during treatment with LUTATHERA.

8 USE IN SPECIFIC POPULATIONS

8.1 Pregnancy

Risk Summary

Based on its mechanism of action, LUTATHERA can cause fetal harm when administered to a pregnant woman [see Clinical Pharmacology (12.1)]. There are no available data on LUTATHERA use in pregnant women. No animal studies using lutetium Lu 177 dotatate have been conducted to evaluate its effect on female reproduction and embryo-fetal development; however, radioactive emissions, including those from LUTATHERA, can cause fetal harm. Advise pregnant women of the potential risk to a fetus.

In the U.S. general population, the estimated background risk of major birth defects and miscarriage in clinically recognized pregnancies is 2% to 4% and 15% to 20%, respectively.

8.2 Lactation

Risk Summary

There are no data on the presence of lutetium Lu 177 dotatate in human milk, or its effects on the breastfed child or milk production. No lactation studies in animals were conducted. Because of the potential risk for serious adverse reactions in breastfed children, advise women not to breastfeed during treatment with LUTATHERA and for 2.5 months after the last dose.

8.3 Females and Males of Reproductive Potential

Based on mechanism of action, LUTATHERA can cause fetal harm when administered to a pregnant woman [see Use in Specific Populations (8.1)].

Pregnancy Testing

Verify pregnancy status of females of reproductive potential prior to initiating LUTATHERA [see Use in Specific Populations (8.1)].

Contraception

Females

Advise females of reproductive potential to use effective contraception during treatment with LUTATHERA and for 7 months after the last dose.

Males

Advise males with female partners of reproductive potential to use effective contraception during treatment with LUTATHERA and for 4 months after the last dose [see Clinical Pharmacology (12.1), Nonclinical Toxicology (13.1)].

Infertility

The recommended cumulative dose of 29.6 GBq of LUTATHERA results in a radiation absorbed dose to the testes and ovaries within the range where temporary or permanent infertility can be expected following external beam radiotherapy [see Dosage and Administration (2.6)].

8.4 Pediatric Use

Somatostatin Receptor-Positive Gastroenteropancreatic Neuroendocrine Tumors

The safety and effectiveness of LUTATHERA have been established in pediatric patients 12 years and older with somatostatin receptor-positive gastroenteropancreatic neuroendocrine tumors (GEP-NETs). Use of LUTATHERA for this indication is supported by evidence from an adequate and well-controlled study of LUTATHERA in adults with additional safety, pharmacokinetic, and dosimetry data in pediatric patients aged 12 years and older with somatostatin receptor-positive tumors, including 4 pediatric patients with GEP-NETs [see Adverse Reactions (6.1), Clinical Pharmacology (12.3), Clinical Studies (14)].

The risks of radiation exposure associated with LUTATHERA are greater in pediatric patients than in adult patients due to longer life expectancy. Continued follow-up is recommended for evaluation of long-term effects.

There was no clinically relevant difference in lutetium Lu 177 dotatate exposure in pediatric patients aged 13 to 16 years versus adult patients [see Clinical Pharmacology (12.3)].

The pharmacokinetic profile and safety of LUTATHERA in pediatric patients 12 years and older with baseline renal impairment have not been studied.

The safety and effectiveness of LUTATHERA have not been established in pediatric patients younger than 12 years old with somatostatin receptor-positive GEP-NETs.

8.5 Geriatric Use

Of the 1325 patients treated with LUTATHERA in clinical trials, 438 patients (33%) were 65 years and older. No overall differences in safety or effectiveness were observed between older and younger patients.

8.6 Renal Impairment

No dose adjustment is recommended for patients with baseline mild to moderate (creatinine clearance 30 to 89 mL/min by Cockcroft-Gault formula) renal impairment. However, patients with baseline mild or moderate renal impairment may be at greater risk of toxicity, including renal toxicity, due to increased radiation exposure. Perform more frequent assessments of renal function in patients with baseline mild to moderate impairment. The pharmacokinetic profile and safety of LUTATHERA in patients with baseline severe renal impairment (creatinine clearance < 30 mL/min by Cockcroft-Gault formula) or end-stage renal disease have not been studied [see Warnings and Precautions (5.4)].

8.7 Hepatic Impairment

No dose adjustment is recommended for patients with baseline mild or moderate hepatic impairment. The pharmacokinetic profile and safety of LUTATHERA in patients with baseline severe hepatic impairment (total bilirubin > 3 times upper limit of normal, regardless of AST level) have not been studied.

11 DESCRIPTION

Lutetium Lu 177 dotatate is a radiolabeled somatostatin analog. The drug substance lutetium Lu 177 dotatate is a cyclic peptide linked with the covalently bound chelator 1,4,7,10-tetraazacyclododecane-1,4,7,10-tetraacetic acid to a radionuclide.

Lutetium Lu 177 dotatate is described as lutetium (Lu 177)-N-[(4,7,10-Tricarboxymethyl-1,4,7,10-tetraazacyclododec-1-yl) acetyl]-D-phenylalanyl-L-cysteinyl-L-tyrosyl-D-tryptophanyl-L-lysyl-L-threoninyl-L-cysteinyl-L-threonine-cyclic (2-7) disulfide. The molecular weight is 1609.6 Daltons and the structural formula is as follows:

LUTATHERA (lutetium Lu 177 dotatate) 370 MBq/mL (10 mCi/mL) Injection is a sterile, clear, colorless to slightly yellow solution for intravenous use. Each single-dose vial contains acetic acid (0.48 mg/mL), sodium acetate (0.66 mg/mL), gentisic acid (0.63 mg/mL), sodium hydroxide (0.64 mg/mL), ascorbic acid (2.8 mg/mL), diethylene triamine pentaacetic acid (0.05 mg/mL), sodium chloride (6.85 mg/mL), and Water for Injection (ad 1 mL). The pH range of the solution is 4.5 to 6.

11.1 Physical Characteristics

Lutetium-177 decays to stable hafnium-177 with a half-life of 6.647 days, by emitting beta-minus radiation with a maximum energy of 0.498 MeV (79%) and photonic radiation (γ) of 0.208 MeV (11%) and 0.113 MeV (6.2%). The main radiations of lutetium-177 are detailed in Table 7.

Table 7. Lutetium-177 Main Radiations
Radiation | Energy (keV) | Iβ^-% | Iγ%
β^- | 176.5 | 12.2
β^- | 248.1 | 0.05
β^- | 384.9 | 9.1
β^- | 497.8 | 78.6
γ | 71.6 |  | 0.15
γ | 112.9 |  | 6.20
γ | 136.7 |  | 0.05
γ | 208.4 |  | 11.0
γ | 249.7 |  | 0.21
γ | 321.3 |  | 0.22

11.2 External Radiation

Table 8 summarizes the radioactive decay properties of lutetium-177.

Table 8. Physical Decay Chart: Lutetium-177 Physical Half-Life = 6.647 Days
Hours | Fraction remaining | Hours | Fraction remaining
0 | 1.000 | 48 (2 days) | 0.812
1 | 0.996 | 72 (3 days) | 0.731
2 | 0.991 | 168 (7 days) | 0.482
5 | 0.979 | 336 (14 days) | 0.232
10 | 0.958 | 720 (30 days) | 0.044
24 (1 day) | 0.901 | 1080 (45 days) | 0.009

12 CLINICAL PHARMACOLOGY

12.1 Mechanism of Action

Lutetium Lu 177 dotatate binds to somatostatin receptors with highest affinity for subtype 2 somatostatin receptors (SSTR2). Upon binding to somatostatin receptor expressing cells, including malignant somatostatin receptor-positive tumors, the compound is internalized. The beta-minus emission from lutetium-177 induces cellular damage by formation of free radicals in somatostatin receptor-positive cells and in neighboring cells.

12.2 Pharmacodynamics

Lutetium Lu 177 dotatate exposure-response relationships and the time course of pharmacodynamics response are unknown.

Cardiac Electrophysiology

The ability of LUTATHERA to prolong the QTc interval at the recommended dose was assessed in an open-label study in 20 patients with somatostatin receptor-positive midgut carcinoid tumors. No large changes in the mean QTc interval (i.e., > 20 ms) were detected.

12.3 Pharmacokinetics

The pharmacokinetics (PK) of lutetium Lu 177 dotatate have been characterized in patients with progressive, somatostatin receptor-positive neuroendocrine tumors. The mean blood exposure (area under the curve) of lutetium Lu 177 dotatate at the recommended dose is 41 ng.h/mL [coefficient of variation (CV) 36%]. The mean maximum blood concentration (Cmax) for lutetium Lu 177 dotatate is 10 ng/mL (CV 50%), which generally occurred at the end of the LUTATHERA infusion.

Distribution

The mean volume of distribution (Vz) for lutetium Lu 177 dotatate is 460 L (CV 54%).

The non-radioactive lutetium Lu 175 dotatate is 43% bound to human plasma proteins.

Within 4 hours after administration, lutetium Lu 177 dotatate distributes in kidneys, tumor lesions, liver, spleen, and, in some patients, pituitary gland and thyroid. The co-administration of amino acids reduced the median radiation dose to the kidneys by 47% (34% to 59%) and increased the mean beta-phase blood clearance of lutetium Lu 177 dotatate by 36%.

Elimination

The mean clearance (CL) is 4.5 L/h (CV 31%) and the mean terminal half-life is 71 (±28) hours for lutetium 177 dotatate.

Metabolism

Lutetium Lu 177 dotatate does not undergo hepatic metabolism.

Excretion

Lutetium Lu 177 dotatate is primarily eliminated renally with cumulative excretion of 44% within 5 hours, 58% within 24 hours, and 65% within 48 hours following LUTATHERA administration. Prolonged elimination of lutetium Lu 177 dotatate in the urine is expected; however, based on the half-life of lutetium-177 and terminal half-life of lutetium Lu 177 dotatate, greater than 99% of the administered radioactivity will be eliminated within 14 days after administration of LUTATHERA [see Warnings and Precautions (5.1)].

Special Populations

Pediatric Patients

There were no clinically relevant differences in exposure of lutetium Lu 177 dotatate in pediatric patients 12 years and older compared to that of adult patients.

Drug Interaction Studies

In Vitro Studies

CYP450 enzymes: The non-radioactive lutetium Lu 175 dotatate is not an inhibitor or inducer of cytochrome P450 (CYP) 1A2, 2B6, 2C9, 2C19 or 2D6 in vitro.

Transporters: The non-radioactive lutetium Lu 175 dotatate is not an inhibitor of P-glycoprotein, BCRP, OAT1, OAT3, OCT1, OCT2, OATP1B1, or OATP1B3 in vitro.

13 NONCLINICAL TOXICOLOGY

13.1 Carcinogenesis, Mutagenesis, Impairment of Fertility

Carcinogenicity and mutagenicity studies have not been conducted with lutetium Lu 177 dotatate; however, radiation is a carcinogen and mutagen.

No animal studies were conducted to determine the effects of lutetium Lu 177 dotatate on fertility.

13.2 Animal Toxicology and/or Pharmacology

The primary target organ in animal studies using the non-radioactive lutetium Lu 175 dotatate was the pancreas, a high SSTR2 expressing organ. Pancreatic acinar apoptosis occurred at lutetium Lu 175 dotatate doses ≥ 5 mg/kg in repeat dose toxicology studies in rats. Pancreatic acinar cell atrophy also occurred in repeat dose toxicology studies in dogs at doses ≥ 500 mcg/kg. These findings were consistent with high uptake of the radiolabeled peptide in the pancreas in animal biodistribution studies.

14 CLINICAL STUDIES

14.1 Progressive, Well-Differentiated Advanced or Metastatic Somatostatin Receptor-Positive Midgut Carcinoid Tumors

The efficacy of LUTATHERA in patients with progressive, well-differentiated, locally advanced/inoperable or metastatic somatostatin receptor-positive midgut carcinoid tumors was established in NETTER-1 (NCT01578239), a randomized, multicenter, open-label, active-controlled trial. Key eligibility criteria included Ki67 index ≤ 20%, Karnofsky performance status ≥ 60, confirmed presence of somatostatin receptors on all lesions (OctreoScan uptake ≥ normal liver), creatinine clearance ≥ 50 mL/min, no prior treatment with peptide receptor radionuclide therapy (PRRT), and no prior external beam radiation therapy to more than 25% of the bone marrow.

At the time of the primary analysis, 229 patients were randomized (1:1) to receive either LUTATHERA 7.4 GBq (200 mCi) every 8 weeks (±1 week) for up to 4 administrations (maximum cumulative dose of 29.6 GBq) or high-dose long-acting octreotide (defined as 60 mg by intramuscular injection every 4 weeks). Patients in the LUTATHERA arm also received long-acting octreotide 30 mg as an intramuscular injection 4 to 24 hours after each LUTATHERA dose and every 4 weeks after completion of LUTATHERA treatment until disease progression or until week 76 of the study. Patients in both arms could receive short-acting octreotide for symptom management; however, short-acting octreotide was withheld at least 24 hours before each LUTATHERA dose. Randomization was stratified by OctreoScan tumor uptake score (Grade 2, 3, or 4) and the length of time that patients had been on the most recent constant dose of octreotide prior to randomization (≤ 6 or > 6 months). The major efficacy outcome measure was progression-free survival (PFS) as determined by a blinded independent review committee (IRC) per RECIST v1.1. Additional efficacy outcome measures were overall response rate (ORR) by IRC, duration of response (DoR) by IRC, and overall survival (OS).

Demographic and baseline disease characteristics were balanced between the treatment arms. Of the 229 patients, 82% were White, 4% were Black, 3% were Hispanic or Latino, 0.4% were Asian, 0.4% were Other, and 9% were not reported. The median age was 64 years (28 to 87 years); 51% were male, 74% had an ileal primary, and 96% had metastatic disease in the liver. The median Karnofsky performance score was 90 (60 to 100), 74% received a constant dose of octreotide for > 6 months and 12% received prior treatment with everolimus. Sixty-nine percent of patients had Ki67 expression in ≤ 2% of tumor cells, 77% had CgA > 2 times the upper limit of normal (ULN), 65% had 5-HIAA > 2 times ULN, and 65% had alkaline phosphatase ≤ ULN.

At the time of the final OS analysis, which occurred 66 months after the primary PFS analysis, 117 patients were randomized to the LUTATHERA arm and 114 patients were randomized to the octreotide arm. In the final OS analysis, there was no statistically significant difference in OS between the two treatment arms.

Efficacy results for NETTER-1 are presented in Table 9 and Figure 1.

Table 9. Efficacy Results in NETTER-1
 | LUTATHERA with long-acting Octreotide (30 mg) N = 116 | Long-acting Octreotide (60 mg) N = 113
PFS by IRC
Events (%) | 27 (23%) | 78 (69%)
Progressive disease, n (%) | 15 (13%) | 61 (54%)
Death, n (%) | 12 (10%) | 17 (15%)
Median in months (95% CI) | NR (18.4, NE) | 8.5 (6.0, 9.1)
Hazard ratioa (95% CI) | 0.21 (0.13, 0.32)
p-valueb | < 0.0001
ORR by IRC
ORR, % (95% CI) | 13% (7%, 19%) | 4% (0.1%, 7%)
Complete response rate, n (%) | 1 (1%) | 0
Partial response rate, n (%) | 14 (12%) | 4 (4%)
p-valuec | 0.0148
Duration of response, median in months (95% CI) | NR (2.8, NE) | 1.9 (1.9, NE)
Abbreviations: CI, confidence interval; IRC, independent radiology committee; NE, not evaluable; NR, not reached; ORR, overall response rate; PFS, progression-free survival.
aHazard ratio based on the unstratified Cox model.
bUnstratified log rank test.
cFisher’s exact test.

Figure 1. Kaplan-Meier Curves for Progression-Free Survival in NETTER-1

14.2 Somatostatin Receptor-Positive Gastroenteropancreatic Neuroendocrine Tumors

The efficacy of LUTATHERA in patients with foregut, midgut, and hindgut gastroenteropancreatic neuroendocrine tumors (GEP-NETs) was assessed in 360 patients in the ERASMUS study. In ERASMUS, LUTATHERA was initially provided as expanded access under a general peptide receptor radionuclide therapy protocol at a single site in the Netherlands. A subsequent LUTATHERA-specific protocol written eight years after study initiation did not describe a specific sample size or hypothesis testing plan but allowed for retrospective data collection. A total of 1214 patients received LUTATHERA in ERASMUS, of whom 578 patients had baseline tumor assessments. Of the 578 patients, 360 (62%) had GEP-NETs and long-term follow-up. Of these 360 patients, 145 (40%) had their tumors prospectively evaluated according to RECIST criteria. LUTATHERA 7.4 GBq (200 mCi) was administered every 6 to 13 weeks for up to 4 doses concurrently with the recommended amino acid solution. The major efficacy outcome was investigator-assessed ORR. The median age in the efficacy subset was 60 years (30 to 85 years), 51% were male, 71% had a baseline Karnofsky performance status ≥ 90, 51% had progressed within 12 months of treatment, and 7% had received prior chemotherapy. Fifty-two percent (52%) of patients received a concomitant somatostatin analog. The median dose of LUTATHERA was 29.6 GBq (800 mCi). The investigator-assessed ORR was 17% (95% CI: 13, 21) based on an analysis that required responders to have had prospective response assessments according to RECIST criteria. Three complete responses were observed (< 1%). Median DoR in the 60 responding patients was 35 months (95% CI: 17, 38).

16 HOW SUPPLIED/STORAGE AND HANDLING

LUTATHERA Injection containing 370 MBq/mL (10 mCi/mL) of lutetium Lu 177 dotatate is a sterile, preservative-free and clear, colorless to slightly yellow solution for intravenous use supplied in a clear, colorless Type I glass 30 mL single-dose vial containing 7.4 GBq (200 mCi) ± 10% of lutetium Lu 177 dotatate at the time of injection (NDC# 69488-003-01). The solution volume in the vial ranges between 20.5 to 25 mL to provide a total of 7.4 GBq (200 mCi) of radioactivity.

The product vial is enclosed within a lead shielded container (NDC# 69488-003-01) placed in a plastic sealed container. The product is shipped in a Type A package.

Store below 25°C (77°F). Do not freeze LUTATHERA. Store in the original package to protect from ionizing radiation (lead shielding).

The shelf life is 72 hours from the date and time of calibration. Discard appropriately at 72 hours.

Lutetium-177 for LUTATHERA may be prepared using two different sources of stable nuclides (either lutetium-176 or ytterbium-176) resulting in different waste management. Consult the documentation provided before using LUTATHERA to ensure appropriate waste management.

17 PATIENT COUNSELING INFORMATION

Risk From Radiation Exposure

Advise patients and/or caregivers to minimize radiation exposure to household contacts during and after treatment with LUTATHERA consistent with institutional good radiation safety practices and patient management procedures [see Dosage and Administration (2.1), Warnings and Precautions (5.1)].

Myelosuppression

Advise patients and/or caregivers to contact their healthcare provider for any signs or symptoms of myelosuppression or infection [see Warnings and Precautions (5.2)].

Secondary Myelodysplastic Syndrome and Leukemia

Advise patients and/or caregivers of the potential for secondary cancers, including myelodysplastic syndrome and acute leukemia [see Warnings and Precautions (5.3)].

Renal Toxicity

Advise patients and/or caregivers to hydrate and to urinate frequently before, on the day of, and the day after administration of LUTATHERA [see Warnings and Precautions (5.4)]. Advise patients to contact their healthcare provider for any signs or symptoms of renal toxicity [see Warnings and Precautions (5.4)].

Hepatotoxicity

Advise patients and/or caregivers of the need for periodic laboratory tests to monitor for hepatotoxicity [see Warnings and Precautions (5.5)]. Advise patients to contact their healthcare provider for any signs or symptoms of hepatotoxicity [see Warnings and Precautions (5.5)].

Hypersensitivity

Advise patients and/or caregivers that LUTATHERA may cause hypersensitivity reactions, including angioedema, and to seek immediate medical attention for signs or symptoms of hypersensitivity [see Warnings and Precautions (5.6)].

Neuroendocrine Hormonal Crises

Advise patients and/or caregivers to contact their healthcare provider for signs or symptoms that may occur following tumor-related hormonal release [see Warnings and Precautions (5.7)].

Embryo-Fetal Toxicity

Advise pregnant women and males and females of reproductive potential of the potential risk to a fetus. Advise females to inform their healthcare provider of a known or suspected pregnancy [see Warnings and Precautions (5.8), Use in Specific Populations (8.1, 8.3)].

Advise females of reproductive potential to use effective contraception during treatment with LUTATHERA and for 7 months after the last dose [see Use in Specific Populations (8.1, 8.3)].

Advise male patients with female partners of reproductive potential to use effective contraception during treatment with LUTATHERA and for 4 months after the last dose [see Use in Specific Populations (8.1, 8.3)].

Lactation

Advise females not to breastfeed during treatment with LUTATHERA and for 2.5 months after the last dose [see Use in Specific Populations (8.2)].

Infertility

Advise female and male patients that LUTATHERA may impair fertility [see Warnings and Precautions (5.9), Use in Specific Populations (8.3)].

Distributed by:
Advanced Accelerator Applications USA, Inc., Millburn, NJ 07041

©2024 Advanced Accelerator Applications USA, Inc.
LUTATHERA® is a registered trademark of Novartis AG and/or its affiliates.

T2024-77

PRINCIPAL DISPLAY PANEL

Lutathera®
lutetium Lu 177 dotatate injection
For Intravenous Infusion
Single-dose vial. Discard after 72 hours.
Rx Only
NDC 69488-003-01

NOVARTIS